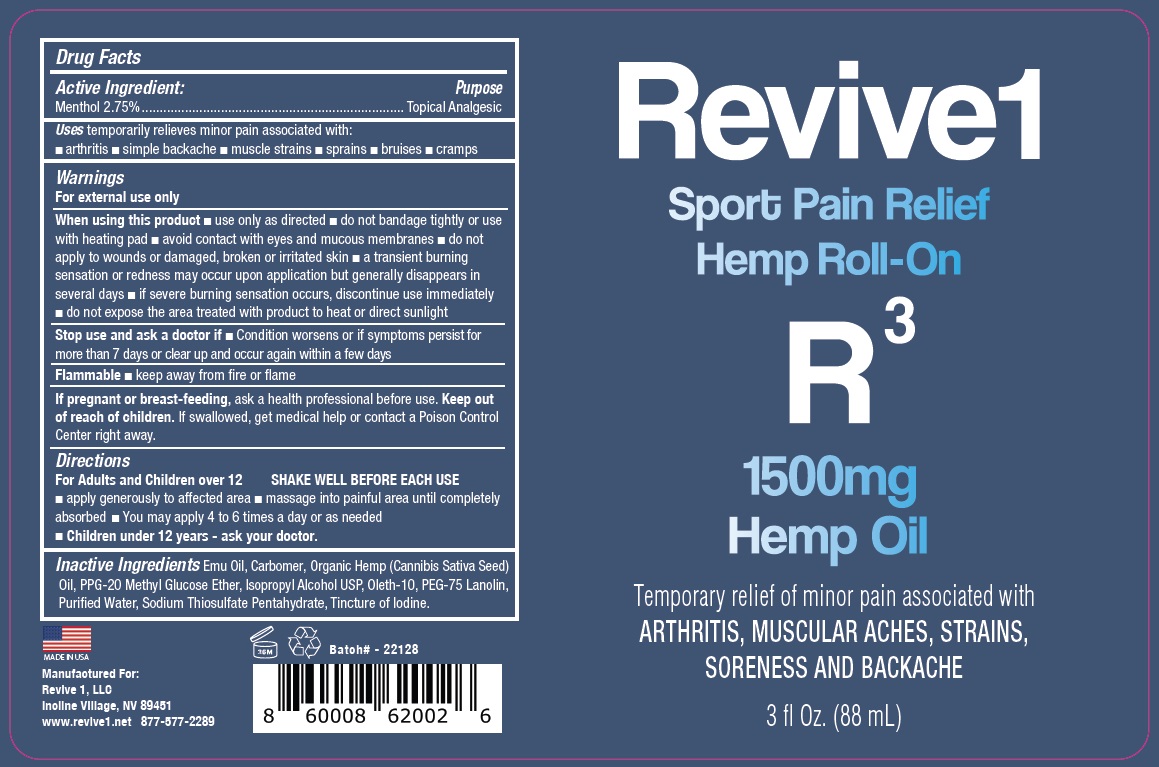 DRUG LABEL: R3
NDC: 69678-348 | Form: LIQUID
Manufacturer: EEZAWAY RELIEF INC
Category: otc | Type: HUMAN OTC DRUG LABEL
Date: 20221109

ACTIVE INGREDIENTS: MENTHOL, UNSPECIFIED FORM 2.75 g/100 mL
INACTIVE INGREDIENTS: EMU OIL; CARBOMER HOMOPOLYMER, UNSPECIFIED TYPE; CANNABIS SATIVA SEED OIL; PPG-20 METHYL GLUCOSE ETHER; ISOPROPYL ALCOHOL; OLETH-10; PEG-75 LANOLIN; WATER; SODIUM THIOSULFATE; IODINE

R^3

Active Ingredient:

Menthol 2.75%

Purpose

Topical Analgesic

Uses

temporarily relieves minor pain associated with:

• arthritis • simple backache • muscle strains • sprains • bruises • cramps

Warnings

For external use only

When using this product • use only as directed • do not bandage tightly or use with heating pad • avoid contact with eyes and mucous membranes • do not apply to wounds or damaged, broken or irritated skin • a transient burning sensation or redness may occur upon application but generally disappears in several days • if severe burning sensation occurs, discontinue use immediately • do not expose the area treated with product to heat or direct sunlight

Stop use and ask a doctor if • Condition worsens or if symptoms persist for more than 7 days or clear up and occur again within a few days

Flammable • keep away from fire or flame

If pregnant or breast-feeding, ask a health professional before use.

Keep out of reach of children. If swallowed, get medical help or contact a Poison Control Center right away.

Directions

For Adults and Children over 12 SHAKE WELL BEFORE EACH USE

• apply generously to affected area • massage into painful area until completely absorbed • You may apply 4 to 6 times a day or as needed

• Children under 12 years - ask your doctor.

Inactive Ingredients

Emu Oil, Carbomer, Organic Hemp (Cannabis Sativa Seed) Oil, PPG-20 Methyl Glucose Ether, Isopropyl Alcohol USP, Oleth-10, PEG-75 Lanolin, Purified Water, Sodium Thiosulfate Pentahydrate, Tincture of Iodine.

Sport Pain Relief Hemp Roll-On

1500mg Hemp Oil

Temporary relief of minor pain associated with ARTHRITIS, MUSCULAR ACHES, STRAINS, SORENESS AND BACKACHE

MADE IN USA

Manufactured For:
Revive 1, LLC
Incline Village, NV 89451
www.revive1.net 877-577-2289